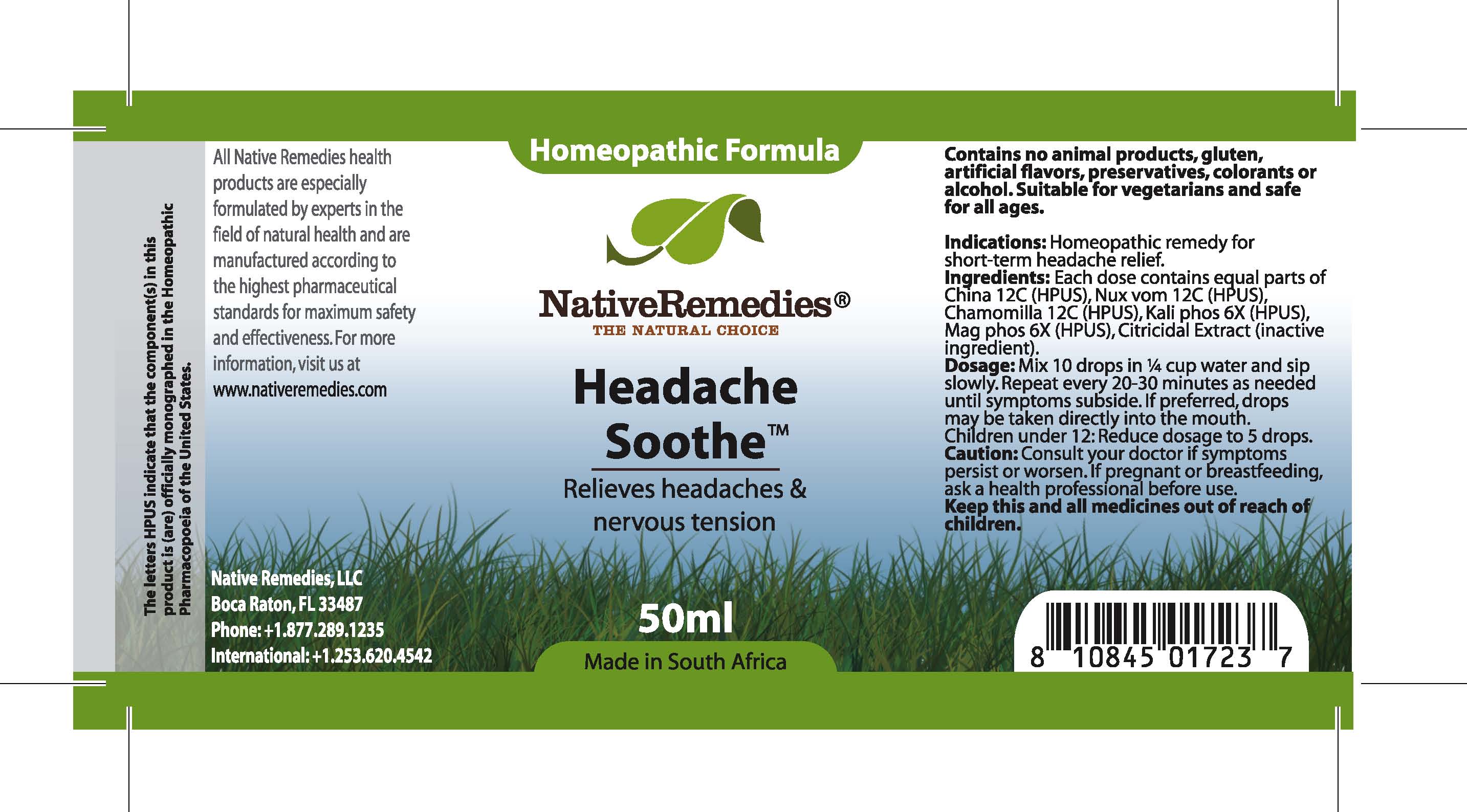 DRUG LABEL: Headache Soothe
NDC: 68647-171 | Form: TINCTURE
Manufacturer: Feelgood Health
Category: homeopathic | Type: HUMAN OTC DRUG LABEL
Date: 20100729

ACTIVE INGREDIENTS: AILANTHUS ALTISSIMA FLOWERING TWIG 12 [hp_C]/40 mL; STRYCHNOS NUX-VOMICA SEED 12 [hp_C]/40 mL; CHAMOMILE 12 [hp_C]/40 mL; POTASSIUM PHOSPHATE, DIBASIC 6 [hp_X]/40 mL; MAGNESIUM PHOSPHATE, DIBASIC TRIHYDRATE 6 [hp_X]/40 mL
INACTIVE INGREDIENTS: WATER 49.486 mL/50 mL

HEADACHE SOOTHE

PURPOSE

Relieves headaches and nervous tension

Indications: Homeopathic remedy for headache relief.

DOSAGE AND ADMINISTRATION

Dosage: Mix 10 drops in ¼ cup water and sip slowly. Repeat every 20-30 minutes as needed until symptoms subside. If preferred, drops may be taken directly into the mouth. Children under 12: Reduce dosage to 5 drops.

GENERAL PRECAUTIONS

Caution: Consult your doctor if symptoms persist or worsen. Keep this and all medicines out of reach of children.

ACTIVE INGREDIENT

Ingredients: Each dose contains equal parts of China (12C) (HPUS), Nux vom (12C) (HPUS), Chamomilla (12C) (HPUS), Kali phos (6X) (HPUS), Mag phos (6X) (HPUS)

Citricidal Extract (inactive ingredient).

PREGNANCY

If pregnant or breastfeeding, ask a health professional before use.

WARNINGS

Contains no animal products, gluten, artificial flavors, preservatives, colorants or alcohol. Suitable for vegetarians and safe for all ages.

PATIENT COUNSELING INFORMATION

All Native Remedies health products are especially formulated by experts in the field of natural health and are manufactured according to the highest pharmaceutical standards for maximum safety and effectiveness. For more information, visit us at www.nativeremedies.com

Distributed by

Native Remedies, LLC

6531 Park of Commerce Blvd.

Suite 160

Boca Raton, FL 33487

Phone: 1.877.289.1235

International: + 1.561.999.8857

The letters HPUS indicate that the component(s) in this product is (are) officially monographed in the Homeopathic Pharmacopoeia of the United States.

KEEP OUT OF REACH OF CHILDREN

Keep this and all medicines out of reach of children.